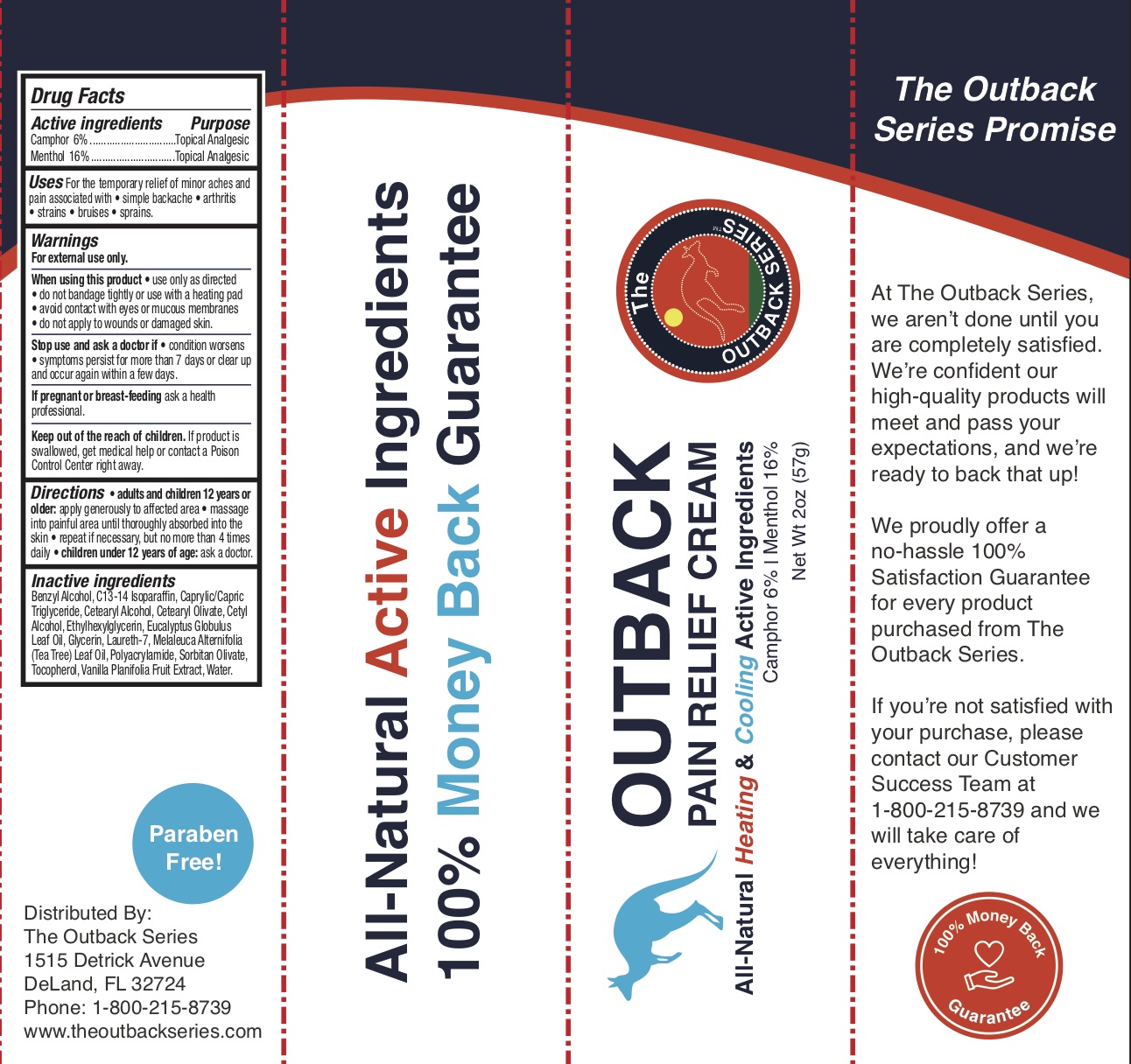 DRUG LABEL: Outback Pain Relief
NDC: 72839-987 | Form: CREAM
Manufacturer: Derma Care Research Labs, LLC
Category: otc | Type: HUMAN OTC DRUG LABEL
Date: 20241220

ACTIVE INGREDIENTS: CAMPHOR (SYNTHETIC) 6 g/100 g; MENTHOL 16 g/100 g
INACTIVE INGREDIENTS: MEDIUM-CHAIN TRIGLYCERIDES; ETHYLHEXYLGLYCERIN; CETOSTEARYL ALCOHOL; WATER; CETYL ALCOHOL; GLYCERIN; EUCALYPTUS GLOBULUS LEAF; TEA TREE OIL; TOCOPHEROL; VANILLA BEAN; CETEARYL OLIVATE; SORBITAN OLIVATE; SODIUM ACRYLOYLDIMETHYLTAURATE-ACRYLAMIDE COPOLYMER (1:1; 90000-150000 MPA.S); BENZYL ALCOHOL; C13-14 ISOPARAFFIN

Outback Pain Relief Liquid Cream

ACTIVE INGREDIENT

Camphor 6%, Menthol 16%

PURPOSE

Topical Analgesic

INDICATIONS AND USAGE

For the temporary relief of minor aches and pain associated with simple backaches, arthritis, strains, bruises, and sprains.

WARNINGS

For external use only. When using this product use only as directed, do not bandage tightly or use with a heating pad, avoid contact with eyes or mucous membranes, and do not apply to wounds or damaged skin. Stop use and ask a doctor if condition worsens, if symptoms persist for more than 7 days or clear up and occur again within a few days.

PREGNANCY OR BREAST FEEDING

If pregnant or breast-feeding ask a health professional.

KEEP OUT OF REACH OF CHILDREN

If swallowed, get medical help or contact a Poison Control Center right away.

DOSAGE AND ADMINISTRATION

Adults and children 12 years of age and older apply generously to the affected area not more than 4 times daily. Children under 12 years of age: ask a doctor.

INACTIVE INGREDIENT

Benzyl Alcohol, C13-14 Isoparaffin, Caprylic/Capric Triglyceride, Cetearyl Alcohol, Cetearyl Olivate, Cetyl Alcohol, Ethylhexylglycerin, Eucalyptus Globulus Leaf Oil, Glycerin, Laureth-7, Melaleuca Alternifolia (Tea Tree) Leaf Oil, Polyacrylamide, Sorbitan Olivate, Tocopherol, Vanilla Planifolia Fruit Extract, Water.